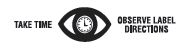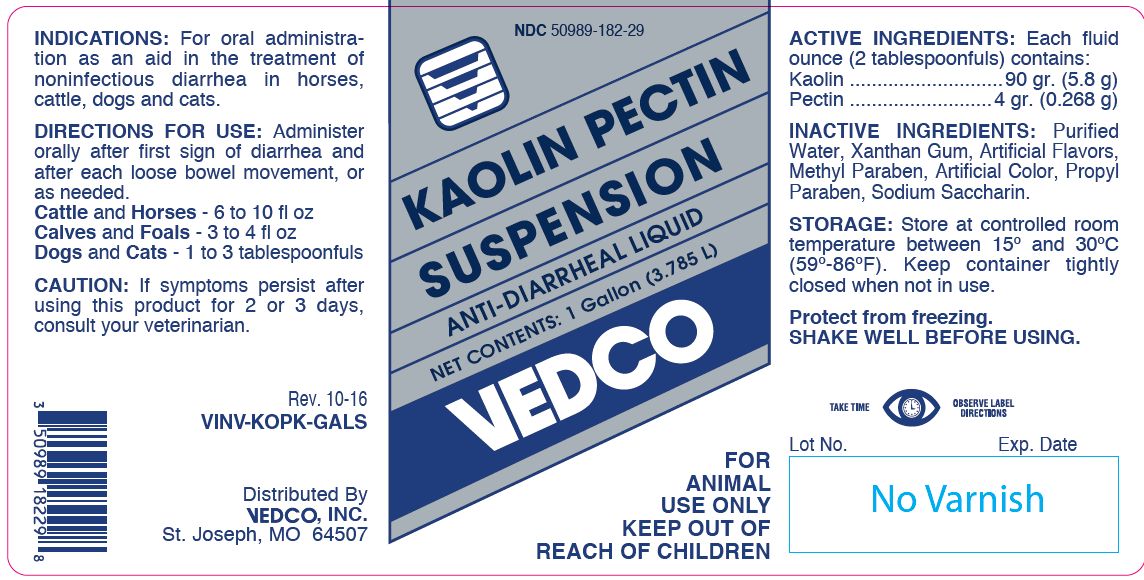 DRUG LABEL: Kaolin Pectin
NDC: 50989-182 | Form: SUSPENSION
Manufacturer: Vedco, Inc.
Category: animal | Type: OTC ANIMAL DRUG LABEL
Date: 20161205

ACTIVE INGREDIENTS: KAOLIN 208.1 g/1 L; PECTIN, CITRUS 8.8 g/1 L

KAOLIN PECTIN SUSPENSION

PURPOSE

ANTI-DIARRHEAL LIQUID

KEEP OUT OF REACH OF CHILDREN

FOR ANIMAL USE ONLY
KEEP OUT OF REACH OF CHILDREN

INDICATIONS:

For oral administration as an aid in the treatment of noninfectious diarrhea in horses, cattle, dogs and cats.

DIRECTIONS FOR USE:

Administer orally after first sign of diarrhea and after each loose bowel movement, or as needed.
Cattle and Horses - 6 to 10 fl oz
Calves and Foals - 3 to 4 fl oz
Dogs and Cats - 1 to 3 tablespoonfuls

CAUTION:

If symptoms persist after using this product for 2 or 3 days, consult your veterinarian.

ACTIVE INGREDIENTS:

Each fluid ounce (2 tablespoonfuls) contains:
Kaolin ............................ 90 gr. (5.8 g)
Pectin .......................... 4 gr. (0.268 g)

INACTIVE INGREDIENTS:

Purified Water, Xanthan Gum, Artificial Flavors, Methyl Paraben, Artificial Color, Propyl Paraben, Sodium Saccharin.

STORAGE:

Store at controlled room temperature between 15º and 30ºC (59º-86ºF). Keep container tightly closed when not in use.

Protect from freezing.
SHAKE WELL BEFORE USING.

NET CONTENTS:

1 Gallon (3.785 L) VINV-KOPK-GALS

INFORMATION FOR OWNERS/CAREGIVERS

Distributed By
VEDCO, INC.
St. Joseph, MO 64507